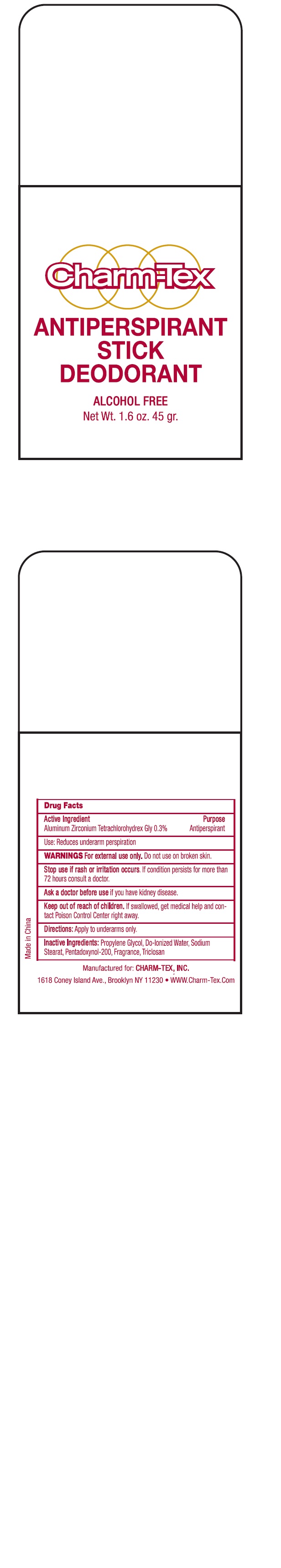 DRUG LABEL: Charm-Tex Antiperspirant Stick Deodorant
NDC: 40057-0002 | Form: SOLUTION
Manufacturer: Charm-tex Inc.
Category: otc | Type: HUMAN OTC DRUG LABEL
Date: 20160720

ACTIVE INGREDIENTS: ALUMINUM ZIRCONIUM TETRACHLOROHYDREX GLY 0.3 g/100 g
INACTIVE INGREDIENTS: WATER; PROPYLENE GLYCOL; SODIUM STEARATE; TRICLOSAN

Active Ingredient: ALUMINUM ZIRCONIUM TETRACHLOROHYDREX GLY

Purpose: Antiperspirant

INDICATIONS AND USAGE

Use: Reduce underarm perspiration

Warning:

For external use only

Do not use on broken skin

Stop use if rash or irritation occurs. If condition persists for more than 72 hours consult a doctor.

Ask a doctor before use if you have kidney disease

Keep out of reach of children. If swallowed, get medical help and contact a Poison Control Center right away.

DOSAGE AND ADMINISTRATION

Directions: Apply to underarm only.

Inactive Ingredients:

Water, Propyleen Glycol, SoDium Stearate, Pentadoxynol-200, Triclosan